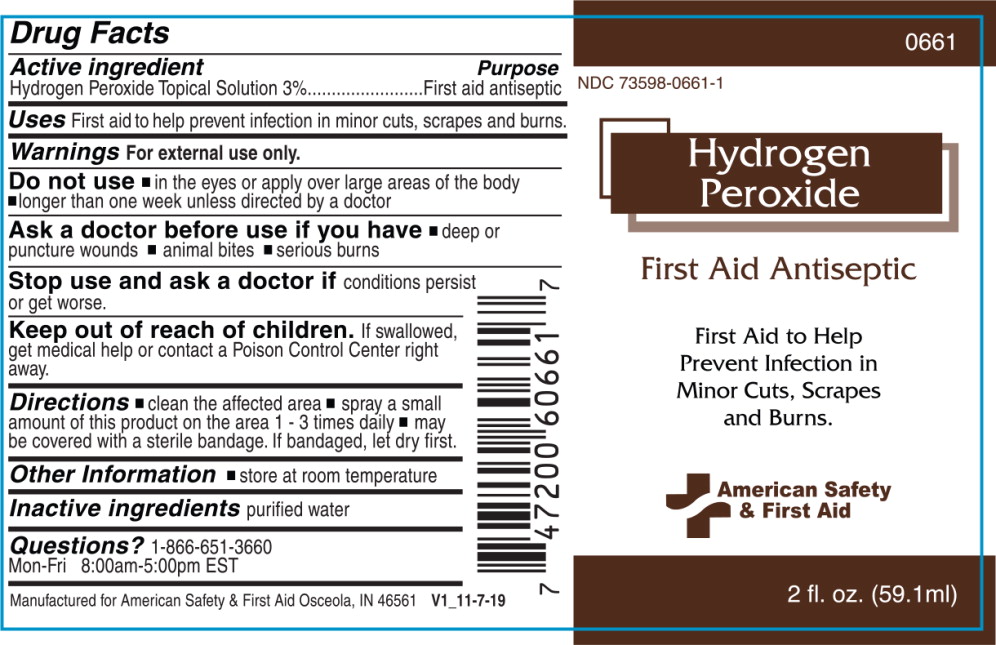 DRUG LABEL: Hydrogen Peroxide
NDC: 73598-0661 | Form: SPRAY
Manufacturer: JHK Inc
Category: otc | Type: HUMAN OTC DRUG LABEL
Date: 20240426

ACTIVE INGREDIENTS: Hydrogen Peroxide 30 mg/1 mL
INACTIVE INGREDIENTS: water

Drug Facts

Active ingredient

Hydrogen Peroxide Topical Solution 3%

Purpose

First aid antiseptic

Uses

First aid to help prevent infection in minor cuts, scrapes and burns.

Warnings

For external use only.

Do not use

- in the eyes or apply over large areas of the body
- longer than one week unless directed by a doctor

Ask a doctor before use if you have

- deep or puncture wounds
- animal bites
- serious burns

Stop use and ask a doctor if conditions persist or get worse.

Keep out of reach of children. If swallowed, get medical help or contact a Poison Control Center right away.

Directions

- clean the affected area
- spray a small amount of this product on the area 1 - 3 times daily
- may be covered with a sterile bandage. If bandaged, let dry first.

Other Information

- store at room temperature

Inactive ingredients

purified water

Questions?

1-866-651-3660

Mon-Fri 8:00am-5:00pm EST

Manufactured for American Safety & First Aid Osceola, IN 46561

V1_11-7-19

Principal Display Panel – Bottle Label

0661

NDC 73598-0661-1

Hydrogen
Peroxide

First Aid Antiseptic

First Aid to Help
Prevent Infection in
Minor Cuts, Scrapes
and Burns.

American Safety
& First Aid

2 fl. oz. (59.1 ml)